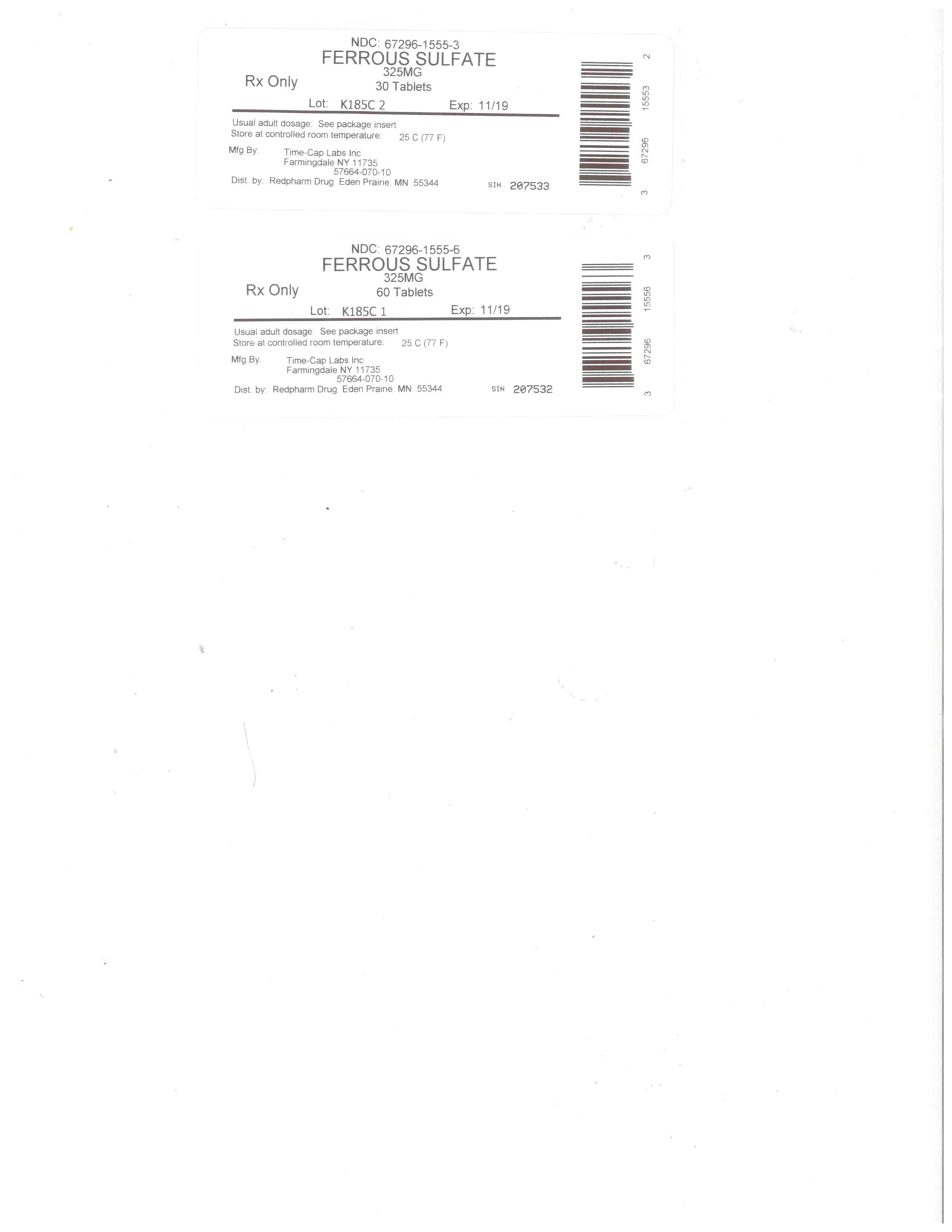 DRUG LABEL: Ferrous Sulfate
NDC: 67296-1555 | Form: TABLET, FILM COATED
Manufacturer: RedPharm Drug, Inc.
Category: otc | Type: HUMAN OTC DRUG LABEL
Date: 20200120

ACTIVE INGREDIENTS: FERROUS SULFATE 325 mg/1 1
INACTIVE INGREDIENTS: POLYETHYLENE GLYCOL 400; TITANIUM DIOXIDE; POLYETHYLENE GLYCOL 8000; CARNAUBA WAX; RIBOFLAVIN; CALCIUM PHOSPHATE, DIBASIC, DIHYDRATE; FD&C BLUE NO. 2; STEARIC ACID; HYPROMELLOSES; FD&C RED NO. 40; MAGNESIUM STEARATE; FD&C BLUE NO. 1; FD&C YELLOW NO. 6; CELLULOSE, MICROCRYSTALLINE; CROSCARMELLOSE SODIUM; SODIUM STARCH GLYCOLATE TYPE A POTATO

ACTIVE INGREDIENT(S)

EACH TABLET CONTAINS:

Amount per tablet Iron 65 mg

% Daily Value 361%

Dried Ferrous Sulfate, equivalent to 325 mg Ferrous Sulfate per tablet.

INACTIVE INGREDIENT SECTIONS

Other ingredients for Red Tablets: microcrystalline cellulose, dibasic calcium phosphate dihydrate, croscarmellose sodium, sodium starch glycolate, hypromellose, stearic acid, polyethylene glycol (PEG) 400, FD&C red #40 aluminum lake, magnesium stearate, titanium dioxide, polyethylene glycol (PEG) 8000, carnauba wax
Other ingredients for Green Tablets: microcrystalline cellulose, dibasic calcium phosphate dihydrate, croscarmellose sodium, sodium starch glycolate, hypromellose, stearic acid, polyethylene glycol (PEG) 400, magnesium stearate, riboflavin, FD&C bule #1 aluminum lake, titanium dioxide, FD&C blue #2 aluminum lake, polyethylene glycol (PEG) 8000, FD&C red #40 aluminum lake, FD&C yellow #6 aluminum lake, carnauba wax

PURPOSE

Dietary Supplement

USE(S)

One tablet daily or as directed by a physician. For children under 12, consult a physician before using this product.

WARNINGS

Iron may interfere with absorpiton of certain antibiotics; these products should not be taken within two hours of each other.
Occasional gastrointestinal discomfort (such as nausea) may be minimized by taking iron with meals. Iron-containing products may occassionally cause constipation or diarrhea. If pregnant or nursing consult a physicial before using this product.

DO NOT USE

TAMPER EVIDENT: DO NOT USE THIS PRODUCT IF THE IMPRINTED FOIL SEAL OVER THE MOUTH OF THE BOTTLE IS CUT, TORN, BROKEN OR MISSING

OTHER REQUIRED WARNINGS

The information on this label has not been evaluated by the Food and Drug Administration. This product is not intended to diagnose, trea, cure or prevent any disease.

To report a serious adverse event or to obtain product information, contact 800-818-4555.

KEEP OUT OF REACH OF CHILDREN

WARNING: Accidental overdose of iron-containing products is a leading cause of fatal poisoning in children under 6. Keep this product out of reach of children. In case of accidental overdose, call a doctor or poison control center immediately.

DIRECTIONS

One tablet daily or as directed by a physician. For children under 12, consult a physical before using this product.
Do not exceed recommended dosage.
Do not use except under the advice and supervision of a physician.

STORAGE

Store at 25˚C (77˚F); excursions permitted between 15˚-30˚C (59˚-86˚F)